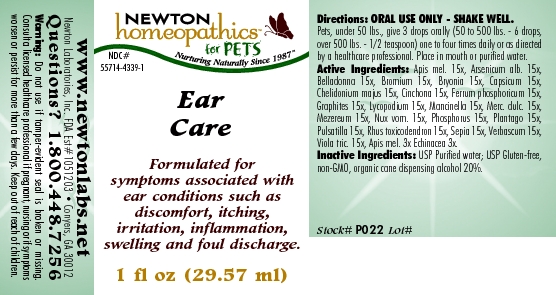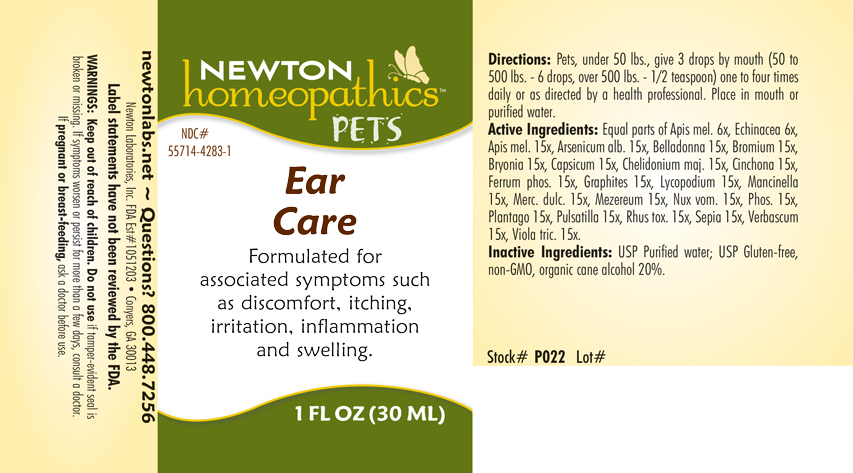 DRUG LABEL: Ear Care
NDC: 55714-4339 | Form: LIQUID
Manufacturer: Newton Laboratories, Inc.
Category: homeopathic | Type: OTC ANIMAL DRUG LABEL
Date: 20190114

ACTIVE INGREDIENTS: Apis Mellifera 15 [hp_X]/1 mL; Arsenic Trioxide 15 [hp_X]/1 mL; Atropa Belladonna 15 [hp_X]/1 mL; Bromine 15 [hp_X]/1 mL; Bryonia Alba Root 15 [hp_X]/1 mL; Capsicum 15 [hp_X]/1 mL; Chelidonium Majus 15 [hp_X]/1 mL; Cinchona Officinalis Bark 15 [hp_X]/1 mL; Ferrosoferric Phosphate 15 [hp_X]/1 mL; Graphite 15 [hp_X]/1 mL; Lycopodium Clavatum Spore 15 [hp_X]/1 mL; Hippomane Mancinella Fruiting Leafy Twig 15 [hp_X]/1 mL; Calomel 15 [hp_X]/1 mL; Daphne Mezereum Bark 15 [hp_X]/1 mL; Strychnos Nux-vomica Seed 15 [hp_X]/1 mL; Phosphorus 15 [hp_X]/1 mL; Plantago Major 15 [hp_X]/1 mL; Pulsatilla Vulgaris 15 [hp_X]/1 mL; Toxicodendron Pubescens Leaf 15 [hp_X]/1 mL; Sepia Officinalis Juice 15 [hp_X]/1 mL; Verbascum Thapsus 15 [hp_X]/1 mL; Viola Tricolor 15 [hp_X]/1 mL; Echinacea, Unspecified 3 [hp_X]/1 mL
INACTIVE INGREDIENTS: Alcohol

Ear Care

INDICATIONS & USAGE SECTION

Formulated for associated symptoms such as discomfort, itching, irritation, inflammation and swelling.

DOSAGE & ADMINISTRATION SECTION

Directions: Pets, under 50 lbs., give 3 drops by mouth (50 to 500 lbs. - 6 drops, over 500 lbs. - 1/2 teaspoon) one to four times daily or as directed by a health professional. Place in mouth or purified water.

OTC - ACTIVE INGREDIENT SECTION

Equal parts of Apis mel. 6x, Echinacea 6x, Apis mel. 15x, Arsenicum alb. 15x, Belladonna 15x, Bromium 15x, Bryonia 15x, Capsicum 15x, Chelidonium majus 15x, Cinchona 15x, Ferrum phos. 15x, Graphites 15x, Lycopodium 15x, Mancinella 15x, Merc. dulc. 15x, Mezereum 15x, Nux vom. 15x, Phos. 15x, Plantago 15x, Pulsatilla 15x, Rhus tox. 15x, Sepia 15x, Verbascum 15x, Viola tric. 15x.

OTC - PURPOSE SECTION

Formulated for associated symptoms such as discomfort, itching, irritation, inflammation and swelling.

INACTIVE INGREDIENT SECTION

USP Purified Water; USP Gluten-free, non-GMO, organic cane alcohol 20%.

QUESTIONS SECTION

newtonlabs.net Questions? 1.800.448.7256
Newton Laboratories, Inc. FDA Est # 1051203 - Conyers, GA 30013

WARNINGS SECTION

Warnings: Keep out of reach of children. Do not use if tamper-evident seal is broken or missing. If symptoms worsen or persist for more than a few days, consult a doctor. If pregnant or breast-feeding, ask a doctor before use.

OTC - PREGNANCY OR BREAST FEEDING SECTION

If pregnant or breast-feeding, ask a doctor before use.

OTC - KEEP OUT OF REACH OF CHILDREN SECTION

Keep out of reach of children.